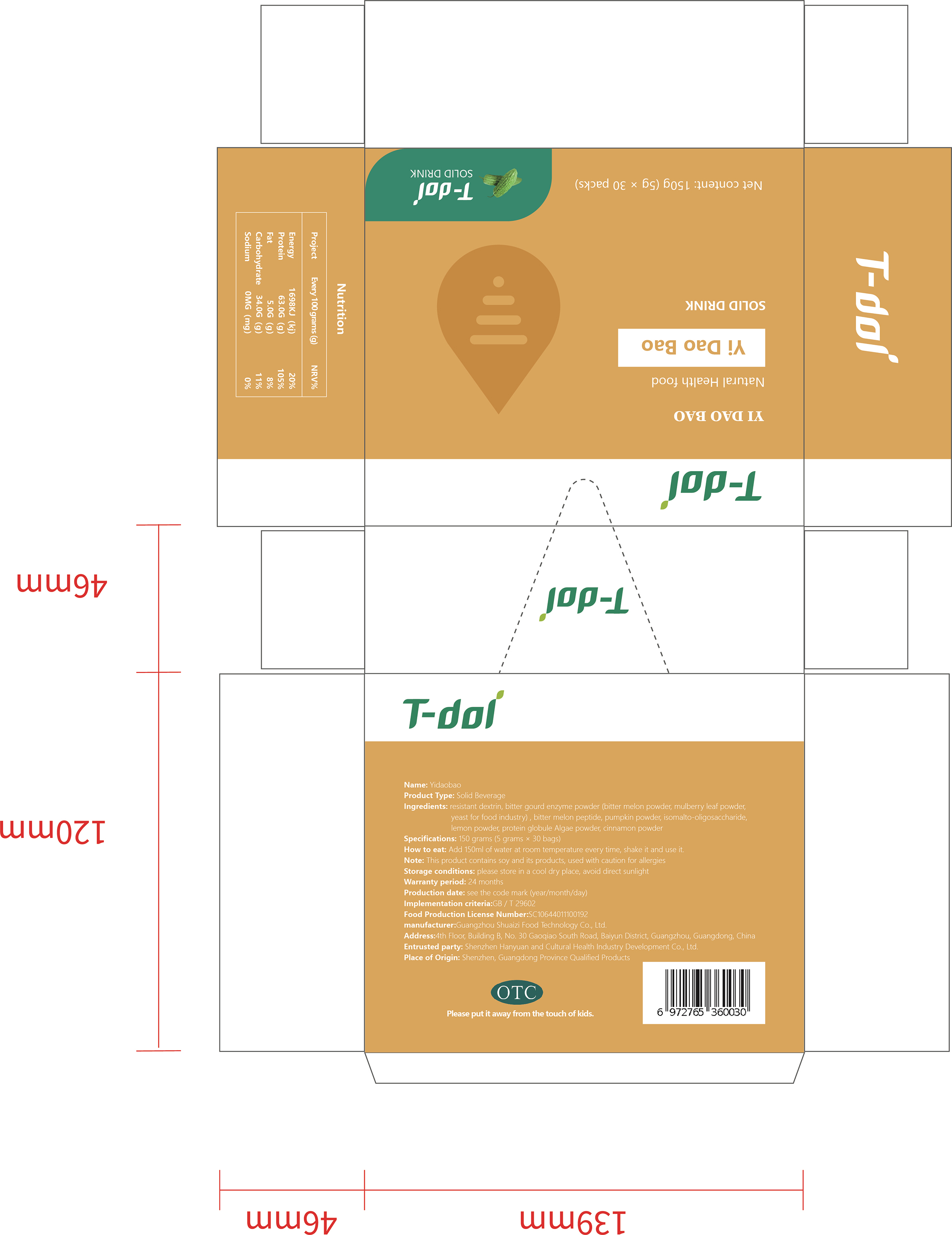 DRUG LABEL: T-dol YI DAO BAO
NDC: 75018-002 | Form: POWDER
Manufacturer: Shenzhen Hanyuanhe Cultural Health Industry Development Co., Ltd.
Category: homeopathic | Type: HUMAN OTC DRUG LABEL
Date: 20191103

ACTIVE INGREDIENTS: MOMORDICA CHARANTIA FRUIT 1.5 g/5 g
INACTIVE INGREDIENTS: CHLORELLA PYRENOIDOSA 0.6 g/5 g; MORUS ALBA LEAF 0.2 g/5 g; CHROMIC CATION 0.45 g/5 g; PUMPKIN 0.6 g/5 g; ZINC CATION 0.45 g/5 g; CINNAMON 0.6 g/5 g; LEMON 0.6 g/5 g

WARNINGS

This product contains soy and its products, used with caution for allergies

INACTIVE INGREDIENT

Mulberry leaf extract, zinc-rich yeast, chromium-rich yeast, pumpkin, cinnamon, chlorella, lemon

KEEP OUT OF REACH OF CHIL DREN SECTION

ACTIVE INGREDIENT

Bitter gourd

DOSAGE AND ADMINISTRATION

Add 150ml of water at room temperature every time, shake it and use it.

INDICATIONS AND USAGE

Add 150ml of water at room temperature every time, shake it and use it.